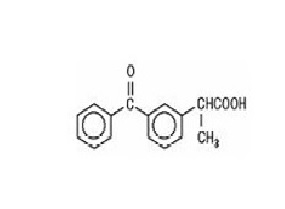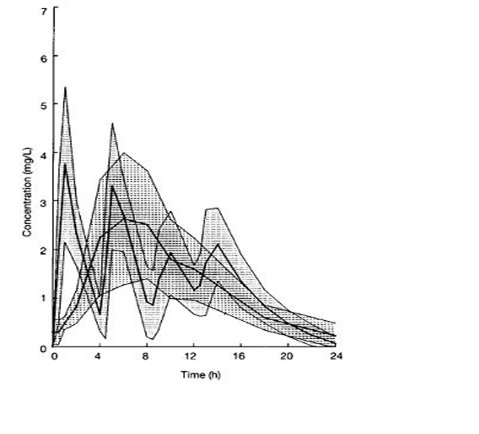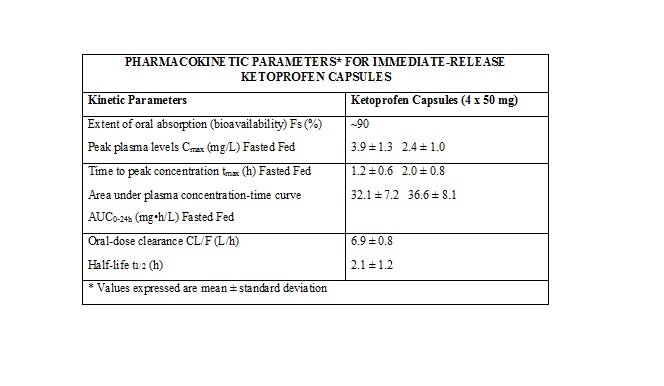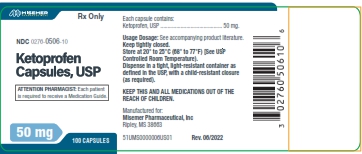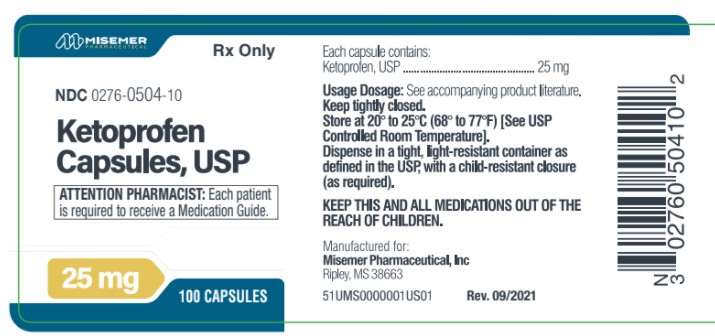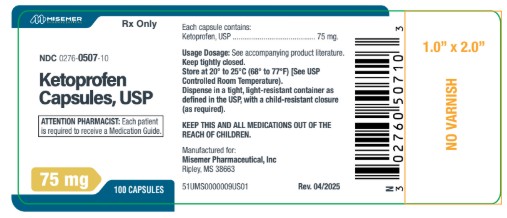 DRUG LABEL: Ketoprofen
NDC: 0276-0507 | Form: CAPSULE
Manufacturer: Misemer Pharmaceuticals, Inc.
Category: prescription | Type: HUMAN PRESCRIPTION DRUG LABEL
Date: 20260215

ACTIVE INGREDIENTS: KETOPROFEN 75 mg/1 1
INACTIVE INGREDIENTS: SILICON DIOXIDE; LACTOSE MONOHYDRATE; MAGNESIUM STEARATE; POVIDONE K30; SODIUM STARCH GLYCOLATE TYPE A POTATO; GELATIN; SODIUM LAURYL SULFATE; TITANIUM DIOXIDE

KETOPROFEN CAPSULES USP

BOXED WARNING

Cardiovascular Thrombotic Events

- Nonsteroidal anti-inflammatory drugs (NSAIDs) cause an increased risk of serious cardiovascular thrombotic events, including myocardial infarction and stroke, which can be fatal. This risk may occur early in treatment and may increase with duration of use.
- Ketoprofen capsules are contraindicated in the setting of coronary artery bypass graft (CABG) surgery.

Gastrointestinal Risk

- NSAIDs cause an increased risk of serious gastrointestinal adverse events including bleeding, ulceration, and perforation of the stomach or intestines, which can be fatal. These events can occur at any time during use and without warning symptoms. Elderly patients are at greater risk for serious gastrointestinal (GI) events.

^1Throughout this package insert, the term NSAID refers to a non-aspirin non-steroidal anti-inflammatory drug.

DESCRIPTION

Ketoprofen is a non-steroidal anti-inflammatory drug. The chemical name for ketoprofen is 2-(3-benzoylphenyl)-propionic acid with the following structural formula:

C16H14O3 M.W. 254.29

It has a pKa of 5.94 in methanol: water (3:1) and an n-octanol: water partition coefficient of 0.97 (buffer pH 7.4).
Ketoprofen is a white or off-white, odorless, nonhygroscopic, fine to granular powder, melting at about 95°C. It is freely soluble in ethanol, chloroform, acetone, ether and soluble in benzene and strong alkali, but practically insoluble in water at 20°C.

Ketoprofen Capsules USP contain 25 mg, 50 mg or 75 mg of Ketoprofen USP for oral administration.

Inactive Ingredients
Drug Product
Colloidal silicon dioxide, lactose monohydrate, magnesium stearate, povidone, sodium starch glycolate.

Capsule Shell Constituents
25 mg: D&C yellow 10, edible printing ink, FD&C blue 1, FD&C yellow 6, gelatin, sodium lauryl
sulfate, and titanium dioxide.
50 mg: D&C yellow 10, edible printing ink, FD&C green 3, gelatin, sodium lauryl sulfate, and
titanium dioxide.
75 mg: Edible printing ink, gelatin, sodium lauryl sulfate and titanium dioxide.

CLINICAL PHARMACOLOGY

Ketoprofen is a non-steroidal anti-inflammatory drug with analgesic and antipyretic properties.
The anti-inflammatory, analgesic and antipyretic properties of ketoprofen have been demonstrated in classical animal and in vitro test systems. In anti-inflammatory models ketoprofen has been shown to have inhibitory effects on prostaglandin and leukotriene synthesis, to have antibradykinin activity, as well as to have lysosomal membrane-stabilizing action. However, its mode of action, like that of other non-steroidal anti-inflammatory drugs, is not fully understood.

Pharmacodynamics
Ketoprofen is a racemate with only the S enantiomer possessing pharmacological activity. The enantiomers have similar concentration time curves and do not appear to interact with one another.
An analgesic effect-concentration relationship for ketoprofen was established in an oral surgery pain study with immediate-release ketoprofen capsules. The effect-site rate constant (ke0) was estimated to be 0.9 hour (95% confidence limits: 0 to 2.1), and the concentration (Ce50) of ketoprofen that produced one-half the maximum PID (pain intensity difference) was 0.3 mcg/mL (95% confidence limits: 0.1 to 0.5). Thirty-three (33) to 68% of patients had an onset of action (as measured by reporting some pain relief) within 30 minutes following a single oral dose in postoperative pain and dysmenorrhea studies. Pain relief (as measured by remedication) persisted for up to 6 hours in 26 to 72% of patients in these studies.

Pharmacokinetics
General
The systemic availability (FS) when the oral formulation is compared with IV administration is approximately 90% in humans. For 75 to 200 mg single doses, the area under the curve has been shown to be dose proportional.
Ketoprofen is > 99% bound to plasma proteins, mainly to albumin.

Absorption
Ketoprofen is rapidly and well-absorbed, with peak plasma levels occurring within 0.5 to 2 hours.

When ketoprofen is administered with food, its total bioavailability (AUC) is not altered; however, the rate of absorption is slowed.
Food intake reduces Cmax by approximately one-half and increases the mean time to peak concentration (tmax) from 1.2 hours for fasting subjects (range, 0.5 to 3 hours) to 2.0 hours for fed subjects (range, 0.75 to 3 hours). The fluctuation of plasma peaks may also be influenced by circadian changes in the absorption process.
Concomitant administration of magnesium hydroxide and aluminum hydroxide does not interfere with absorption of ketoprofen from ketoprofen capsules.
Multiple Dosing
Steady-state concentrations of ketoprofen are attained within 24 hours after commencing treatment with immediate-release ketoprofen capsules. In studies with healthy male volunteers, trough levels at 24 hours following administration of immediate-release ketoprofen 50 mg capsules QID for 12 hours were 0.07 mg/L and 0.13 mg/L at 24 hours following administration of immediate-release ketoprofen 75 mg capsules TID for 12 hours. Thus, relative to the peak plasma concentration, the accumulation of ketoprofen after multiple doses of immediate-release ketoprofen capsules is minimal.
The figure below shows a reduction in peak height and area after the second 50 mg dose. This is probably due to a combination of food effects, circadian effects, and plasma sampling times. It is unclear to what extent each factor contributes to the loss of peak height and area.
The shaded area represents ± 1 standard deviation (S.D.) around the mean for immediate-release ketoprofen capsules.

KETOPROFEN PLASMA CONCENTRATIONS IN SUBJECTS RECEIVING KETOPROFEN CAPSULES 50 MG EVERY 4 HOURS FOR 16 HOURS

Metabolism
The metabolic fate of ketoprofen is glucuronide conjugation to form an unstable acyl-glucuronide. The glucuronic acid moiety can be converted back to the parent compound. Thus, the metabolite serves as a potential reservoir for parent drug, and this may be important in persons with renal insufficiency, whereby the conjugate may accumulate in the serum and undergo deconjugation back to the parent drug (see Special Populations, Renally Impaired). The conjugates are reported to appear only in trace amounts in plasma in healthy adults, but are higher in elderly subjects-presumably because of reduced renal clearance. It has been demonstrated that in elderly subjects following multiple doses (50 mg every 6 h), the ratio of conjugated to parent ketoprofen AUC was 30% and 3%, respectively, for the S & R enantiomers.
There are no known active metabolites of ketoprofen. Ketoprofen has been shown not to induce drug-metabolizing enzymes.

Elimination
The plasma clearance of ketoprofen is approximately 0.08 L/kg/h with a Vd of 0.1 L/kg after IV administration. The elimination half-life of ketoprofen has been reported to be 2.05 ± 0.58 h (Mean ± S.D.) following IV administration from 2 to 4 hours following administration of ketoprofen capsules. In cases of slow drug absorption, the elimination rate is dependent on the absorption rate and thus t1/2 relative to an IV dose appears prolonged.
In a 24 hour period, approximately 80% of an administered dose of ketoprofen is excreted in the urine, primarily as the glucuronide metabolite.

Enterohepatic recirculation of the drug has been postulated, although biliary levels have never been measured to confirm this.

Special Populations
Elderly
Clearance and unbound fraction
The plasma and renal clearance of ketoprofen is reduced in the elderly (mean age, 73 years) compared to a younger normal population (mean age, 27 years). Hence, ketoprofen peak concentration and AUC increase with increasing age. In addition, there is a corresponding increase in unbound fraction with increasing age. Data from one trial suggest that the increase is greater in women than in men. It has not been determined whether age-related changes in absorption among the elderly contribute to the changes in bioavailability of ketoprofen.
In a study conducted with young and elderly men and women, results for subjects older than 75 years of age showed that free drug AUC increased by 40% and Cmax increased by 60% as compared with estimates of the same parameters in young subjects (those younger than 35 years of age;.
Also in the elderly, the ratio of intrinsic clearance/availability decreased by 35% and plasma half-life was prolonged by 26%. This reduction is thought to be due to a decrease in hepatic extraction associated with aging.
Renally Impaired
Studies of the effects of renal-function impairment have been small. They indicate a decrease in clearance in patients with impaired renal function. In 23 patients with renal impairment, free ketoprofen peak concentration was not significantly elevated, but free ketoprofen clearance was reduced from 15 L/kg/h for normal subjects to 7 L/kg/h in patients with mildly impaired renal function, and to 4 L/kg/h in patients with moderately to severely impaired renal function. The elimination t1/2 was prolonged from 1.6 hours in normal subjects to approximately 3 hours in patients with mild renal impairment, and to approximately 5 to 9 hours in patients with moderately to severely impaired renal function.
Hepatically Impaired
For patients with alcoholic cirrhosis, no significant changes in the kinetic disposition of immediate-release ketoprofen capsules were observed relative to age-matched normal subjects: the plasma clearance of drug was 0.07 L/kg/h in 26 hepatically impaired patients. The elimination half-life was comparable to that observed for normal subjects. However, the unbound (biologically active) fraction was approximately doubled, probably due to hypoalbuminemia and high variability which was observed in the pharmacokinetics for cirrhotic patients. Therefore, these patients should be carefully monitored and daily doses of ketoprofen kept at the minimum providing the desired therapeutic effect.

Clinical Trials
Rheumatoid Arthritis and Osteoarthritis
The efficacy of ketoprofen has been demonstrated in patients with rheumatoid arthritis and osteoarthritis. In other trials, ketoprofen demonstrated effectiveness comparable to aspirin, ibuprofen, naproxen, piroxicam, diclofenac, and indomethacin. In some of these studies there were more dropouts due to gastrointestinal side effects among patients on ketoprofen than among patients on other NSAIDs.
In studies with patients with rheumatoid arthritis, ketoprofen was administered in combination with gold salts, antimalarials, low-dose methotrexate, d-penicillamine, and/or corticosteroids with results comparable to those seen with control non-steroidal drugs.

Management of Pain
The effectiveness of immediate-release ketoprofen capsules as a general-purpose analgesic has been studied in standard pain models which have shown the effectiveness of doses of 25 to 150 mg. Doses of 25 mg were superior to placebo. Doses larger than 25 mg generally could not be shown to be significantly more effective, but there was a tendency toward faster onset and greater duration of action with 50 mg, and, in the case of dysmenorrhea, a significantly greater effect overall with 75 mg. Doses greater than 50 to 75 mg did not have increased analgesic effect. Studies in postoperative pain have shown that ketoprofen in doses of 25 to 100 mg was comparable to 650 mg of acetaminophen with 60 mg of codeine, or 650 mg of acetaminophen with 10 mg of oxycodone. Ketoprofen tended to be somewhat slower in onset; peak pain relief was about the same and the duration of the effect tended to be 1 to 2 hours longer, particularly with the higher doses of ketoprofen.

INDICATIONS AND USAGE

Carefully consider the potential benefits and risks of ketoprofen capsules USP and other treatment options before deciding to use ketoprofen capsules USP. Use the lowest effective dose for the shortest duration consistent with individual patient treatment goals.
Ketoprofen capsules USP are indicated for the management of the signs and symptoms of rheumatoid arthritis and osteoarthritis.
Ketoprofen capsules USP are indicated for the management of pain. Ketoprofen capsules USP are also indicated for treatment of primary dysmenorrhea.

CONTRAINDICATIONS

Ketoprofen capsules are contraindicated in patients who have shown hypersensitivity to ketoprofen.
Ketoprofen capsules USP should not be given to patients who have experienced asthma, urticaria, or allergic-type reactions after taking aspirin or other NSAIDs. Severe, rarely fatal, anaphylactic reactions to ketoprofen have been reported in such patients.
Ketoprofen capsules are contraindicated in the setting of coronary artery bypass graft (CABG) surgery.

WARNINGS

Cardiovascular Effects
Cardiovascular Thrombotic Events
Clinical trials of several COX-2 selective and nonselective NSAIDs of up to three years duration have shown an increased risk of serious cardiovascular (CV) thrombotic events, including myocardial infarction (MI) and stroke, which can be fatal. Based on available data, it is unclear that the risk for CV thrombotic events is similar for all NSAIDs. The relative increase in serious CV thrombotic events over baseline conferred by NSAID use appears to be similar in those with and without known CV disease or risk factors for CV disease. However, patients with known CV disease or risk factors had a higher absolute incidence of excess serious CV thrombotic events, due to their increased baseline rate. Some observational studies found that this increased risk of serious CV thrombotic events began as early as the first weeks of treatment. The increase in CV thrombotic risk has been observed most consistently at higher doses.
To minimize the potential risk for an adverse CV event in NSAID-treated patients, use the lowest effective dose for the shortest duration possible. Physicians and patients should remain alert for the development of such events, throughout the entire treatment course, even in the absence of previous CV symptoms. Patients should be informed about the symptoms of serious CV events and the steps to take if they occur.
There is no consistent evidence that concurrent use of aspirin mitigates the increased risk of serious CV thrombotic events associated with NSAID use. The concurrent use of aspirin and an NSAID, such as Ketoprofen, increases the risk of serious gastrointestinal (GI) events.

Status Post Coronary Artery Bypass Graft (CABG) Surgery
Two large, controlled clinical trials of a COX-2 selective NSAID for the treatments of pain in the first 10-14 days following CABG surgery found an increased incidence of myocardial infarction and stroke. NSAIDs are contraindicated in the setting of CABG.

Post-MI Patients
Observational studies conducted in the Danish National Registry have demonstrated that patients treated with NSAIDs in the post-MI period were at increased risk of reinfarction, CV-related death, and all-cause mortality beginning in the first week of treatment. In this same cohort, the incidence of death in the first year post MI was 20 per 100 person years in NSAID-treated patients compared to 12 per 100 person years in non-NSAID exposed patients. Although the absolute rate of death declined somewhat after the first year post-MI, the increased relative risk of death in NSAID users persisted over at least the next four years of follow-up.
Avoid the use of Ketoprofen capsules in patients with a recent MI unless the benefits are expected to outweigh the risk of recurrent CV thrombotic events. If Ketoprofen capsules are used in patients with a recent MI, monitor patients for signs of cardiac ischemia.

Hypertension
NSAIDs, including ketoprofen capsules, can lead to onset of new hypertension or worsening of preexisting hypertension, either of which may contribute to the increased incidence of CV events. Patients taking thiazides or loop diuretics may have impaired response to these therapies when taking NSAIDs. NSAIDs, including ketoprofen capsules, should be used with caution in patients with hypertension. Blood pressure (BP) should be monitored closely during the initiation of NSAID treatment and throughout the course of therapy.

Heart Failure and Edema
The Coxib and traditional NSAID Trialists’ Collaboration meta-analysis of randomized controlled trials demonstrated an approximately two-fold increase in hospitalizations for heart failure in COX-2 selective-treated patients and nonselective NSAID-treated patients compared to placebo-treated patients. In a Danish National Registry study of patients with heart failure, NSAID use increased the risk of MI, hospitalization for heart failure, and death.
Additionally, fluid retention and edema have been observed in some patients treated with NSAIDs. Use of Ketoprofen may blunt the CV effects of several therapeutic agents used to treat these medical conditions [e.g., diuretics, ACE inhibitors, or angiotensin receptor blockers (ARBs)].
Avoid the use of Ketoprofen capsules in patients with severe heart failure unless the benefits are expected to outweigh the risk of worsening heart failure. If Ketoprofen capsules are used in patients with severe heart failure, monitor patients for signs of worsening heart failure.

Gastrointestinal Effects - Risk of Ulceration, Bleeding, and Perforation
NSAIDs, including ketoprofen capsules, can cause serious gastrointestinal (GI) adverse events including inflammation, bleeding, ulceration, and perforation, of the stomach, small intestine, or large intestine, which can be fatal. These serious adverse events can occur at any time, with or without warning symptoms, in patients treated with NSAIDs. Only one in five patients, who develop a serious upper GI adverse event on NSAID therapy, is symptomatic. Upper GI ulcers, gross bleeding, or perforation caused by NSAIDs occur in approximately 1% of patients treated for 3 to 6 months, and in about 2 to 4% of patients treated for one year. These trends continue with longer duration of use, increasing the likelihood of developing a serious GI event at some time during the course of therapy. However, even short-term therapy is not without risk.
NSAIDs should be prescribed with extreme caution in those with a prior history of ulcer disease or gastrointestinal bleeding. Patients with a prior history of peptic ulcer disease and/or gastrointestinal bleeding who use NSAIDs have a greater than 10 fold increased risk for developing a GI bleed compared to patients with neither of these risk factors. Other factors that increase the risk for GI bleeding in patients treated with NSAIDs include concomitant use of oral corticosteroids or anticoagulants, longer duration of NSAID therapy, smoking, use of alcohol, older age, and poor general health status. Most spontaneous reports of fatal GI events are in elderly or debilitated patients and therefore, special care should be taken in treating this population.
To minimize the potential risk for an adverse GI event in patients treated with an NSAID, the lowest effective dose should be used for the shortest possible duration. Patients and physicians should remain alert for signs and symptoms of GI ulceration and bleeding during NSAID therapy and promptly initiate additional evaluation and treatment if a serious GI adverse event is suspected. This should include discontinuation of the NSAID until a serious GI adverse event is ruled out.Forhigh risk patients, alternate therapies that do not involve NSAIDs should be considered.

Renal Effects
Long-term administration of NSAIDs has resulted in renal papillary necrosis and other renal injury. Renal toxicity has also been seen in patients in whom renal prostaglandins have a compensatory role in the maintenance of renal perfusion. In these patients, administration of a non-steroidal anti-inflammatory drug may cause a dose-dependent reduction in prostaglandin formation and, secondarily, in renal blood flow, which may precipitate overt renal decompensation. Patients at greater risk of this reaction are those with impaired renal function, heart failure, liver dysfunction, those taking diuretics and ACE-inhibitors, and the elderly. Discontinuation of NSAID therapy is usually followed by recovery to the pretreatment state.

Advanced Renal Disease
No information is available from controlled clinical studies regarding the use of ketoprofen capsules in patients with advanced renal disease. Therefore, treatment with ketoprofen capsules is not recommended in these patients with advanced renal disease. If ketoprofen capsule therapy must be initiated, close monitoring of the patient's renal function is advisable.

Anaphylactoid Reactions
As with other NSAIDs, anaphylactoid reactions may occur in patients without known prior
exposure to ketoprofen capsules. Ketoprofen capsules should not be given to patients with the
aspirin triad. This symptom complex typically occurs in asthmatic patients who experience rhinitis
with or without nasal polyps, or who exhibit severe, potentially fatal bronchospasm after taking
aspirin or other NSAIDs (see CONTRAINDICATIONS and PRECAUTIONS, Preexisting Asthma).
Emergency help should be sought in cases where an anaphylactoid reaction occurs.

Serious Skin Reactions
NSAIDs, including ketoprofen capsules, can cause serious skin adverse events such as exfoliative dermatitis, Stevens-Johnson syndrome (SJS), and toxic epidermal necrolysis (TEN), which can be fatal. fatal. NSAIDs can also cause fixed drug eruption (FDE). FDE may present as a more severe variant known as generalized bullous fixed drug eruption (GBFDE), which can be life-threatening. These serious events may occur without warning. Inform patients about the signs and symptoms of serious skin reactions, and to discontinue the use of Ketoprofen Capsules, USP at the first appearance of skin rash or any other sign of
hypersensitivity. Ketoprofen Capsules, USP is contraindicated in patients with previous serious skin reactions to NSAIDs (see CONTRAINDICATIONS).

Drug Reaction with Eosinophilia and Systemic Symptoms (DRESS)
Drug Reaction with Eosinophilia and Systemic Symptoms (DRESS) has been reported in
patients taking NSAIDs such as ketoprofen capsules. Some of these events have been fatal
or life-threatening. DRESS typically, although not exclusively, presents with fever, rash,
lymphadenopathy, and/or facial swelling. Other clinical manifestations may include hepatitis,
nephritis, hematological abnormalities, myocarditis, or myositis. Sometimes symptoms of DRESS
may resemble an acute viral infection. Eosinophilia is often present. Because this disorder is
variable in its presentation, other organ systems not noted here may be involved. It is important
to note that early manifestations of hypersensitivity, such as fever or lymphadenopathy, may
be present even though rash is not evident. If such signs or symptoms are present, discontinue
ketoprofen capsules and evaluate the patient immediately.
Fetal Toxicity
Premature Closure of Fetal Ductus Arteriosus:
Avoid use of NSAIDs, including ketoprofen capsules, in pregnant women at about 30 weeks
gestation and later. NSAIDs including ketoprofen capsules, increase the risk of premature closure
of the fetal ductus arteriosus at approximately this gestational age.

Oligohydramnios/Neonatal Renal Impairment:
Use of NSAIDs, including ketoprofen capsules, at about 20 weeks gestation or later in pregnancy
may cause fetal renal dysfunction leading to oligohydramnios and, in some cases, neonatal renal
impairment. These adverse outcomes are seen, on average, after days to weeks of treatment,
although oligohydramnios has been infrequently reported as soon as 48 hours after NSAID
initiation. Oligohydramnios is often, but not always, reversible with treatment discontinuation.
Complications of prolonged oligohydramnios may, for example, include limb contractures and
delayed lung maturation. In some postmarketing cases of impaired neonatal renal function,
invasive procedures such as exchange transfusion or dialysis were required.

If NSAID treatment is necessary between about 20 weeks and 30 weeks gestation, limit
ketoprofen capsules use to the lowest effective dose and shortest duration possible. Consider
ultrasound monitoring of amniotic fluid if ketoprofen capsules treatment extends beyond 48
hours. Discontinue ketoprofen capsules if oligohydramnios occurs and follow up according to
clinical practice [see PRECAUTIONS; Pregnancy].

PRECAUTIONS

General
Ketoprofen capsules cannot be expected to substitute for corticosteroids or to treat corticosteroid insufficiency. Abrupt discontinuation of corticosteroids may lead to disease exacerbation. Patients on prolonged corticosteroid therapy should have their therapy tapered slowly if a decision is made to discontinue corticosteroids.

If steroid dosage is reduced or eliminated during therapy, it should be reduced slowly and the patients observed closely for any evidence of adverse effects, including adrenal insufficiency and exacerbation of symptoms of arthritis.
The pharmacological activity of ketoprofen capsules in reducing fever and inflammation may diminish the utility of these diagnostic signs in detecting complications of presumed noninfectious, painful conditions.
Ketoprofen and other non-steroidal anti-inflammatory drugs cause nephritis in mice and rats associated with chronic administration. Rare cases of interstitial nephritis or nephrotic syndrome have been reported in humans with ketoprofen since it has been marketed.
A second form of renal toxicity has been seen in patients with conditions leading to a reduction in renal blood flow or blood volume, where renal prostaglandins have a supportive role in the maintenance of renal blood flow. In these patients, administration of a non-steroidal anti-inflammatory drug results in a dose-dependent decrease in prostaglandin synthesis and, secondarily, in renal blood flow which may precipitate overt renal failure. Patients at greatest risk of this reaction are those with impaired renal function, heart failure, liver dysfunction, those taking diuretics, and the elderly. Discontinuation of non-steroidal anti-inflammatory drug therapy is typically followed by recovery to the pretreatment state.
Since ketoprofen is primarily eliminated by the kidneys and its pharmacokinetics are altered by renal failure (see CLINICAL PHARMACOLOGY), patients with significantly impaired renal function should be closely monitored, and a reduction of dosage should be anticipated to avoid accumulation of ketoprofen and/or its metabolites (see DOSAGE AND ADMINISTRATION).

Hepatic Effects
Borderline elevations of one or more liver tests may occur in up to 15% of patients taking NSAIDs including ketoprofen capsules. These laboratory abnormalities may progress, may remain unchanged, or may be transient with continuing therapy. Notable elevations of ALT or AST (approximately three or more times the upper limit of normal) have been reported in approximately 1% of patients in clinical trials with NSAIDs. In addition, rare cases of severe hepatic reactions, including jaundice, and fatal fulminant hepatitis, liver necrosis and hepatic failure, some of them with fatal outcomes have been reported.
A patient with symptoms and/or signs suggesting liver dysfunction, or in whom an abnormal liver test has occurred, should be evaluated for evidence of the development of a more severe hepatic reaction while on therapy with ketoprofen capsules. If clinical signs and symptoms consistent with liver disease develop, or if systemic manifestations occur (e.g., eosinophilia, rash, etc.), ketoprofen capsules should be discontinued.
In patients with chronic liver disease with reduced serum albumin levels, ketoprofen’s pharmacokinetics are altered (see CLINICAL PHARMACOLOGY). Such patients should be closely monitored, and a reduction of dosage should be anticipated to avoid high blood levels of ketoprofen and/or its metabolites (see DOSAGE AND ADMINISTRATION).

Hematological Effects
Anemia is sometimes seen in patients receiving NSAIDs, including ketoprofen capsules. This may be due to fluid retention, occult or gross GI blood loss, or an incompletely described effect upon erythropoiesis. Patients on long-term treatment with NSAIDs, including ketoprofen capsules, should have their hemoglobin or hematocrit checked if they exhibit any signs or symptoms of anemia.
NSAIDs inhibit platelet aggregation and have been shown to prolong bleeding time in some patients. Unlike aspirin, their effect on platelet function is quantitatively less, of shorter duration, and reversible. Patients receiving ketoprofen capsules who may be adversely affected by alterations in platelet function, such as those with coagulation disorders or patients receiving anticoagulants, should be carefully monitored.

Preexisting Asthma
Patients with asthma may have aspirin-sensitive asthma. The use of aspirin in patients with aspirin-sensitive asthma has been associated with severe bronchospasm which can be fatal. Since cross reactivity, including bronchospasm, between aspirin and other non-steroidal anti-inflammatory drugs has been reported in such aspirin-sensitive patients, ketoprofen capsules should not be administered to patients with this form of aspirin sensitivity and should be used with caution in patients with preexisting asthma.

Information for Patients

Patients should be informed of the following information before initiating therapy with an NSAID and periodically during the course of ongoing therapy. Patients should also be encouraged to read the NSAID Medication Guide that accompanies each prescription dispensed.

1. Cardiovascular Thrombotic Events
Advise patients to be alert for the symptoms of cardiovascular thrombotic events, including chest pain, shortness of breath, weakness, or slurring of speech, and to report any of these symptoms to their health care provider immediately [see Warnings].
2. Ketoprofen capsules, like other NSAIDs, can cause GI discomfort and, rarely, serious GI side effects, such as ulcers and bleeding, which may result in hospitalization and even death. Although serious GI tract ulcerations and bleeding can occur without warning symptoms, patients should be alert for the signs and symptoms of ulcerations and bleeding, and should ask for medical advice when observing any indicative signs or symptoms including epigastric pain, dyspepsia, melena, and hematemesis. Patients should be apprised of the importance of this follow-up (see WARNINGS, Gastrointestinal Effects - Risk of Ulceration, Bleeding, and Perforation).
3. Serious Skin Reactions, including DRESS
Advise patients to stop taking ketoprofen capsules immediately if they develop any type of rash
or fever and to contact their healthcare provider as soon as possible [see Warnings].
4. Heart Failure and Edema
Advise patients to be alert for the symptoms of congestive heart failure including shortness of breath, unexplained weight gain, or edema and to contact their healthcare provider if such symptoms occur. [see Warnings].
5. Patients should be informed of the warning signs and symptoms of hepatotoxicity (e.g., nausea, fatigue, lethargy, pruritus, jaundice, right upper quadrant tenderness, and "flu-like" symptoms). If these occur, patients should be instructed to stop therapy and seek immediate medical therapy.
6. Patients should be informed of the signs of an anaphylactoid reaction (e.g., difficulty breathing, swelling of the face or throat). If these occur, patients should be instructed to seek immediate emergency help (see WARNINGS).
7. Fetal Toxicity
Inform pregnant women to avoid use of ketoprofen capsules and other NSAIDs starting at 30
weeks gestation because of the risk of the premature closing of the fetal ductus arteriosus.
If treatment with ketoprofen capsules is needed for a pregnant woman between about 20 to
30 weeks gestation, advise her that she may need to be monitored for oligohydramnios, if
treatment continues for longer than 48 hours [see WARNINGS; Fetal Toxicity, PRECAUTIONS;
Pregnancy].

NSAIDs are often essential agents in the management of arthritis and have a major role in the
treatment of pain, but they also may be commonly employed for conditions which are less
serious. Physicians may wish to discuss with their patients the potential risks (see WARNINGS,
PRECAUTIONS, and ADVERSE REACTIONS) and likely benefits of NSAID treatment, particularly
when the drugs are used for less serious conditions where treatment without NSAIDs may
represent an acceptable alternative to both the patient and physician.

Because aspirin causes an increase in the level of unbound ketoprofen, patients should be advised not to take aspirin while taking ketoprofen (see Drug Interactions). It is possible that minor adverse symptoms of gastric intolerance may be prevented by administering ketoprofen capsules with antacids, food, or milk. Because food and milk do affect the rate but not the extent of absorption (see CLINICAL PHARMACOLOGY), physicians may want to make specific recommendations to patients about when they should take ketoprofen in relation to food and/or what patients should do if they experience minor GI symptoms associated with ketoprofen therapy.

Laboratory Tests

Because serious GI tract ulcerations and bleeding can occur without warning symptoms, physicians should monitor for signs or symptoms of GI bleeding. Patients on long-term treatment with NSAIDs, should have their CBC and a chemistry profile checked periodically. If clinical signs and symptoms consistent with liver or renal disease develop, systemic manifestations occur (e.g., eosinophilia, rash, etc.) or if abnormal liver tests persist or worsen, ketoprofen capsules should be discontinued.

Drug Interactions

The following drug interactions were studied with ketoprofen doses of 200 mg/day. The possibility of increased interaction should be kept in mind when ketoprofen capsule doses greater than 50 mg as a single dose or 200 mg of ketoprofen per day are used concomitantly with highly bound drugs.
ACE-inhibitors
Reports suggest that NSAIDs may diminish the antihypertensive effect of ACE-inhibitors. This interaction should be given consideration in patients taking NSAIDs concomitantly with ACE-inhibitors.

Antacids
Concomitant administration of magnesium hydroxide and aluminum hydroxide does not interfere with the rate or extent of the absorption of ketoprofen administered as ketoprofen capsules.

Aspirin
Ketoprofen does not alter aspirin absorption; however, in a study of 12 normal subjects, concurrent administration of aspirin decreased ketoprofen protein binding and increased ketoprofen plasma clearance from 0.07 L/kg/h without aspirin to 0.11 L/kg/h with aspirin. The clinical significance of these changes is not known; however, as with other NSAIDs, concomitant administration of ketoprofen and aspirin is not generally recommended because of the potential of increased adverse effects.

Diuretics
NSAIDs can reduce the natriuretic effect of furosemide and thiazides in some patients. Hydrochlorothiazide, given concomitantly with ketoprofen, produces a reduction in urinary potassium and chloride excretion compared to hydrochlorothiazide alone. Patients taking diuretics are at a greater risk of developing renal failure secondary to a decrease in renal blood flow caused by prostaglandin inhibition (see PRECAUTIONS). During concomitant therapy with NSAIDs, the patient should be observed closely for signs of renal failure (see WARNINGS, Renal Effects), as well as to assure diuretic efficacy.

Digoxin
In a study in 12 patients with congestive heart failure where ketoprofen and digoxin were concomitantly administered, ketoprofen did not alter the serum levels of digoxin.

Lithium
NSAIDs have produced an elevation of plasma lithium levels and a reduction in renal lithium clearance. The mean minimum lithium concentration increased 15% and the renal clearance was decreased by approximately 20%. These effects have been attributed to inhibition of renal prostaglandin synthesis by the NSAID. Thus, when NSAIDs and lithium are administered concurrently, subjects should be observed carefully for signs of lithium toxicity.

Methotrexate
Ketoprofen, like other NSAIDs, may cause changes in the elimination of methotrexate leading to elevated serum levels of the drug and increased toxicity. NSAIDs have been reported to competitively inhibit methotrexate accumulation in rabbit kidney slices. This may indicate that they could enhance the toxicity of methotrexate. Caution should be used when NSAIDs are administered concomitantly with methotrexate.

Probenecid
Probenecid increases both free and bound ketoprofen by reducing the plasma clearance of ketoprofen to about one-third, as well as decreasing its protein binding. Therefore, the combination of ketoprofen and probenecid is not recommended.

Warfarin
The effects of warfarin and NSAIDs on GI bleeding are synergistic, such that users of both drugs together have a risk of serious GI bleeding higher than users of either drug alone. In a short-term controlled study in 14 normal volunteers, ketoprofen did not significantly interfere with the effect of warfarin on prothrombin time. Bleeding from a number of sites may be a complication of warfarin treatment and GI bleeding a complication of ketoprofen treatment. Because prostaglandins play an important role in hemostasis and ketoprofen has an effect on platelet function as well (see Drug/Laboratory Test Interactions, Effect on Blood Coagulation), concurrent therapy with ketoprofen and warfarin requires close monitoring of patients on both drugs.

DRUG & OR LABORATORY TEST INTERACTIONS

Effect on Blood Coagulation
Ketoprofen decreases platelet adhesion and aggregation. Therefore, it can prolong bleeding time by approximately 3 to 4 minutes from baseline values. There is no significant change in platelet count, prothrombin time, partial thromboplastin time, or thrombin time.

Carcinogenesis, Mutagenesis, Impairment of Fertility

Chronic oral toxicity studies in mice (up to 32 mg/kg/day; 96 mg/m^2/day) did not indicate a carcinogenic potential for ketoprofen. The maximum recommended human therapeutic dose is 300 mg/day for a 60 kg patient with a body surface area of 1.6 m^2, which is 5 mg/kg/day or 185 mg/m^2/day. Thus the mice were treated at 0.5 times the maximum human daily dose based on surface area.
A 2 year carcinogenicity study in rats, using doses up to 6.0 mg/kg/day (36 mg/m^2/day), showed no evidence of tumorigenic potential. All groups were treated for 104 weeks except the females receiving 6.0 mg/kg/day (36 mg/m^2/day) where the drug treatment was terminated in week 81 because of low survival; the remaining rats were sacrificed after week 87. Their survival in the groups treated for 104 weeks was within 6% of the control group. An earlier 2 year study with doses up to 12.5 mg/kg/day (75 mg/m^2/day) also showed no evidence of tumorigenicity, but the survival rate was low and the study was therefore judged inconclusive. Ketoprofen did not show mutagenic potential in the Ames Test. Ketoprofen administered to male rats (up to 9 mg/kg/day; or 54 mg/m^2/day) had no significant effect on reproductive performance or fertility. In female rats administered 6 or 9 mg/kg/day (36 or 54 mg/m^2/day), a decrease in the number of implantation sites has been noted. The dosages of 36 mg/m^2/day in rats represent 0.2 times the maximum recommended human dose of 185 mg/m^2/day (see above).
Abnormal spermatogenesis or inhibition of spermatogenesis developed in rats and dogs at high doses, and a decrease in the weight of the testes occurred in dogs and baboons at high doses.

Pregnancy

Risk Summary
Use of NSAIDs, including ketoprofen capsules, can cause premature closure of the fetal ductus
arteriosus and fetal renal dysfunction leading to oligohydramnios and, in some cases, neonatal
renal impairment. Because of these risks, limit dose and duration of ketoprofen capsules use
between about 20 and 30 weeks of gestation, and avoid ketoprofen capsules use at about 30
weeks of gestation and later in pregnancy [see WARNINGS; Fetal Toxicity].

Premature Closure of Fetal Ductus Arteriosus
Use of NSAIDs, including ketoprofen capsules, at about 30 weeks gestation or later in pregnancy
increases the risk of premature closure of the fetal ductus arteriosus.

Oligohydramnios/Neonatal Renal Impairment
Use of NSAIDs at about 20 weeks gestation or later in pregnancy has been associated with
cases of fetal renal dysfunction leading to oligohydramnios, and in some cases, neonatal renal
impairment.
Data from observational studies regarding other potential embryofetal risks of NSAID use in
women in the first or second trimesters of pregnancy are inconclusive. In animal reproduction
studies ketoprofen administered to mice at doses up to 12 mg/kg/day (36 mg/m2
/day) and rats at

doses up to 9 mg/kg/day (54 mg/m2

/day), the approximate equivalent of 0.2 times the maximum

recommended therapeutic dose of 185 mg/m2

/day, showed no teratogenic or embryotoxic effects.
In separate studies in rabbits, maternally toxic doses were associated with embryotoxicity but
not teratogenicity. However, animal reproduction studies are not always predictive of human
response. Based on animal data, prostaglandins have been shown to have an important role in
endometrial vascular permeability, blastocyst implantation, and decidualization. In animal studies,
administration of prostaglandin synthesis inhibitors such as ketoprofen, resulted in increased
pre- and post-implantation loss. Prostaglandins also have been shown to have an important role
in fetal kidney development. In published animal studies, prostaglandin synthesis inhibitors have
been reported to impair kidney development when administered at clinically relevant doses.
The estimated background risk of major birth defects and miscarriage for the indicated
population(s) is unknown. All pregnancies have a background risk of birth defect, loss, or other
adverse outcomes. In the U.S. general population, the estimated background risk of major birth
defects and miscarriage in clinically recognized pregnancies is 2-4% and 15-20%, respectively.

Clinical Considerations
Fetal/Neonatal Adverse Reactions
Premature Closure of Fetal Ductus Arteriosus:
Avoid use of NSAIDs in women at about 30 weeks gestation and later in pregnancy, because
NSAIDs, including ketoprofen capsules, can cause premature closure of the fetal ductus arteriosus
(see WARNINGS; Fetal Toxicity).
Oligohydramnios/Neonatal Renal Impairment
If an NSAID is necessary at about 20 weeks gestation or later in pregnancy, limit the use to the
lowest effective dose and shortest duration possible. If ketoprofen capsules treatment extends
beyond 48 hours, consider monitoring with ultrasound for oligohydramnios. If oligohydramnios
occurs, discontinue ketoprofen capsules and follow up according to clinical practice (see
WARNINGS; Fetal Toxicity).

Data
Human Data
Premature Closure of Fetal Ductus Arteriosus:
Published literature reports that the use of NSAIDs at about 30 weeks of gestation and later in
pregnancy may cause premature closure of the fetal ductus arteriosus.
Oligohydramnios/Neonatal Renal Impairment:
Published studies and postmarketing reports describe maternal NSAID use at about 20 weeks
gestation or later in pregnancy associated with fetal renal dysfunction leading to oligohydramnios,
and in some cases, neonatal renal impairment. These adverse outcomes are seen, on average,
after days to weeks of treatment, although oligohydramnios has been infrequently reported as
soon as 48 hours after NSAID initiation. In many cases, but not all, the decrease in amniotic fluid
was transient and reversible with cessation of the drug. There have been a limited number of case
reports of maternal NSAID use and neonatal renal dysfunction without oligohydramnios, some
of which were irreversible. Some cases of neonatal renal dysfunction required treatment with
invasive procedures, such as exchange transfusion or dialysis.
Methodological limitations of these postmarketing studies and reports include lack of a control
group; limited information regarding dose, duration, and timing of drug exposure; and concomitant
use of other medications. These limitations preclude establishing a reliable estimate of the risk of
adverse fetal and neonatal outcomes with maternal NSAID use. Because the published safety data
on neonatal outcomes involved mostly preterm infants, the generalizability of certain reported
risks to the full-term infant exposed to NSAIDs through maternal use is uncertain.

Labor and Delivery

The effects of ketoprofen on labor and delivery in pregnant women are unknown. Studies in rats have shown ketoprofen at doses of 6 mg/kg (36 mg/m^2/day, approximately equal to 0.2 times the maximum recommended human dose) prolongs pregnancy when given before the onset of labor. Because of the known effects of prostaglandin-inhibiting drugs on the fetal cardiovascular system (closure of ductus arteriosus), use of ketoprofen during late pregnancy should be avoided.

Nursing Mothers

It is not known whether this drug is excreted in human milk. Data on secretion in human milk after ingestion of ketoprofen do not exist. In rats, ketoprofen at doses of 9 mg/kg (54 mg/m2/day; approximately 0.3 times the maximum human therapeutic dose) did not affect perinatal development. Upon administration to lactating dogs, the milk concentration of ketoprofen was found to be 4 to 5% of the plasma drug level. As with other drugs that are excreted in milk, ketoprofen is not recommended for use in nursing mothers.

Pediatric Use

Safety and effectiveness in pediatric patients below the age of 18 have not been established.

Geriatric Use

As with any NSAIDs, caution should be exercised in treating the elderly (65 years and older). In pharmacokinetic studies, ketoprofen clearance was reduced in older patients receiving ketoprofen capsules, compared with younger patients. Peak ketoprofen concentrations and free drug AUC were increased in older patients (see Special Populations). The glucuronide conjugate of ketoprofen, which can serve as a potential reservoir for the parent drug, is known to be substantially excreted by the kidney. Because elderly patients are more likely to have decreased renal function, care should be taken in dose selection. It is recommended that the initial dosage of ketoprofen capsules should be reduced for patients over 75 years of age and it may be useful to monitor renal function (see DOSAGE AND ADMINISTRATION). In addition, the risk of toxic reactions to this drug may be greater in patients with impaired renal function. Elderly patients may be more sensitive to the antiprostaglandin effects of NSAIDs (on the gastrointestinal tract and kidneys) than younger patients (see WARNINGS and PRECAUTIONS). In particular, elderly or debilitated patients who receive NSAID therapy seem to tolerate gastrointestinal ulceration or bleeding less well than other individuals, and most spontaneous reports of fatal GI events are in this population. Therefore, caution should be exercised in treating the elderly, and when individualizing their dosage, extra care should be taken when increasing the dose (see DOSAGE AND ADMINISTRATION).
In ketoprofen capsule clinical studies involving a total of 1540 osteoarthritis or rheumatoid arthritis patients, 369 (24%) were ≥ 65 years of age, and 92 (6%) were ≥ 75 years of age. For ketoprofen capsule acute pain studies, 23 (5%) of 484 patients were ≥ 60 years of age. No overall differences in effectiveness were observed between these patients and younger patients.

ADVERSE REACTIONS

The incidence of common adverse reactions (above 1%) was obtained from a population of 835 ketoprofen-treated patients in double-blind trials lasting from 4 to 54 weeks and in 622 patients treated with ketoprofen extended-release capsules in trials lasting from 4 to 16 weeks.
Minor gastrointestinal side effects predominated; upper gastrointestinal symptoms were more common than lower gastrointestinal symptoms. In crossover trials in 321 patients with rheumatoid arthritis or osteoarthritis, there was no difference in either upper or lower gastrointestinal symptoms between patients treated with 200 mg of ketoprofen extended-release capsules once a day or 75 mg of ketoprofen immediate-release capsules TID (255 mg/day). Peptic ulcer or GI bleeding occurred in controlled clinical trials in less than 1% of 1,076 patients; however, in open label continuation studies in 1,292 patients, the rate was greater than 2%.
The incidence of peptic ulceration in patients on NSAIDs is dependent on many risk factors including age, sex, smoking, alcohol use, diet, stress, concomitant drugs such as aspirin and corticosteroids, as well as the dose and duration of treatment with NSAIDs (see WARNINGS).
Gastrointestinal reactions were followed in frequency by central nervous system side effects, such as headache, dizziness, or drowsiness. The incidence of some adverse reactions appears to be dose-related (see DOSAGE AND ADMINISTRATION). Rare adverse reactions (incidence less than 1%) were collected from one or more of the following sources: foreign reports to manufacturers and regulatory agencies, publications, U.S. clinical trials, and/or U.S. postmarketing spontaneous reports.
Reactions are listed below under body system, then by incidence or number of cases in decreasing incidence.

Incidence Greater Than 1% (Probable Causal Relationship)
Digestive: Dyspepsia (11%), nausea*, abdominal pain*, diarrhea*, constipation*, flatulence*, anorexia, vomiting, stomatitis.
Nervous System: Headache*, dizziness, CNS inhibition (i.e., pooled reports of somnolence, malaise, depression, etc.) or excitation (i.e., insomnia, nervousness, dreams, etc.)*.
Special Senses: Tinnitus, visual disturbance.
Skin and Appendages: Rash.
Urogenital: Impairment of renal function (edema, increased BUN)*, signs or symptoms of urinary-tract irritation.
* Adverse events occurring in 3 to 9% of patients.

Incidence Less Than 1% (Probable Causal Relationship)
Body as a Whole: Chills, facial edema, infection, pain, allergic reaction, anaphylaxis.
Cardiovascular: Hypertension, palpitation, tachycardia, congestive heart failure, peripheral vascular disease, vasodilation.
Digestive: Appetite increased, dry mouth, eructation, gastritis, rectal hemorrhage, melena, fecal occult blood, salivation, peptic ulcer, gastrointestinal perforation, hematemesis, intestinal ulceration, hepatic dysfunction, hepatitis, cholestatic hepatitis, jaundice.
Hemic: Hypocoagulability, agranulocytosis, anemia, hemolysis, purpura, thrombocytopenia.
Metabolic and Nutritional: Thirst, weight gain, weight loss, hyponatremia.
Musculoskeletal: Myalgia.
Nervous System: Amnesia, confusion, impotence, migraine, paresthesia, vertigo.
Respiratory: Dyspnea, hemoptysis, epistaxis, pharyngitis, rhinitis, bronchospasm, laryngeal edema.
Skin and Appendages: Alopecia, eczema, pruritus, purpuric rash, sweating, urticaria, bullous rash, exfoliative dermatitis, photosensitivity, skin discoloration, onycholysis, toxic epidermal necrolysis, erythema multiforme, Stevens-Johnson syndrome.and fixed drug eruption (FDE)
Special Senses: Conjunctivitis, conjunctivitis sicca, eye pain, hearing impairment, retinal hemorrhage and pigmentation change, taste perversion.
Urogenital: Menometrorrhagia, hematuria, renal failure, interstitial nephritis, nephrotic syndrome.

To report SUSPECTED ADVERSE REACTIONS, contact Misemer Pharmaceutical, Inc. at

1-662-993-9625 or FDA at 1-800-FDA-1088 or www.fda.gov/medwatch.

Incidence Less Than 1% (Causal Relationship Unknown)

The following rare adverse reactions, whose causal relationship to ketoprofen is uncertain, are being listed to serve as alerting information to the physician.
Body as a Whole: Septicemia, shock.
Cardiovascular: Arrhythmias, myocardial infarction.
Digestive: Buccal necrosis, ulcerative colitis, microvesicular steatosis, pancreatitis.
Endocrine: Diabetes mellitus (aggravated).
Nervous System: Dysphoria, hallucination, libido disturbance, nightmares, personality disorder, aseptic meningitis.
Urogenital: Acute tubulopathy, gynecomastia

OVERDOSAGE

Signs and symptoms following acute NSAID overdose are usually limited to lethargy, drowsiness, nausea, vomiting, and epigastric pain, which are generally reversible with supportive care. Respiratory depression, coma, or convulsions have occurred following large ketoprofen overdoses. Gastrointestinal bleeding, hypotension, hypertension, or acute renal failure may occur, but are rare.
Patients should be managed by symptomatic and supportive care following an NSAID overdose. There are no specific antidotes. Gut decontamination may be indicated in patients with symptoms seen within 4 hours or following a large overdose (5 to 10 times the usual dose). This should be accomplished via emesis and/or activated charcoal (60 to 100 g in adults, 1 to 2 g/kg in children) with a saline cathartic or sorbitol added to the first dose. Forced diuresis, alkalinization of the urine, hemodialysis or hemoperfusion would probably not be useful due to ketoprofen’s high protein binding.
Case reports include twenty-six overdoses: 6 were in children, 16 in adolescents, and 4 in adults. Five of these patients had minor symptoms (vomiting in 4, drowsiness in 1 child). A 12-year-old girl had tonic-clonic convulsions 1 to 2 hours after ingesting an unknown quantity of ketoprofen and 1 or 2 tablets of acetaminophen with hydrocodone. Her ketoprofen level was 1128 mg/L (56 times the upper therapeutic level of 20 mg/L) 3 to 4 hours post ingestion. Full recovery ensued 18 hours after ingestion following management with intubation, diazepam, and activated charcoal. A 45-year-old woman ingested twelve 200 mg extended-release ketoprofen capsules and 375 mL vodka, was treated with emesis and supportive measures 2 hours after ingestion, and recovered completely with her only complaint being mild epigastric pain.

DOSAGE AND ADMINISTRATION

Carefully consider the potential benefits and risks of ketoprofen capsules and other treatment options before deciding to use ketoprofen capsules. Use the lowest effective dose for the shortest duration consistent with individual patient treatment goals (see WARNINGS).
After observing the response to initial therapy with ketoprofen capsules, the dose and frequency should be adjusted to suit an individual patient's needs.
Concomitant use of ketoprofen capsules and ketoprofen extended-release capsules is not recommended.
If minor side effects appear, they may disappear at a lower dose which may still have an adequate therapeutic effect. If well tolerated but not optimally effective, the dosage may be increased. Individual patients may show a better response to 300 mg of ketoprofen capsules daily as compared to 200 mg, although in well-controlled clinical trials patients on 300 mg did not show greater mean effectiveness. They did, however, show an increased frequency of upper- and lower-GI distress and headaches. It is of interest that women also had an increased frequency of these adverse effects compared to men. When treating patients with 300 mg/day, the physician should observe sufficient increased clinical benefit to offset potential increased risk.
In patients with mildly impaired renal function, the maximum recommended total daily dose of ketoprofen capsules is 150 mg. In patients with a more severe renal impairment (GFR less than 25 mL/min/1.73 m2 or end-stage renal impairment), the maximum total daily dose of ketoprofen capsules should not exceed 100 mg.
In elderly patients, renal function may be reduced with apparently normal serum creatinine and/or BUN levels. Therefore, it is recommended that the initial dosage of ketoprofen capsules should be reduced for patients over 75 years of age (see Geriatric Use).
It is recommended that for patients with impaired liver function and serum albumin concentration less than 3.5 g/dL, the maximum initial total daily dose of ketoprofen capsules should be 100 mg. All patients with metabolic impairment, particularly those with both hypoalbuminemia and reduced renal function, may have increased levels of free (biologically active) ketoprofen and should be closely monitored. The dosage may be increased to the range recommended for the general population, if necessary, only after good individual tolerance has been ascertained.
Because hypoalbuminemia and reduced renal function both increase the fraction of free drug (biologically active form), patients who have both conditions may be at greater risk of adverse effects. Therefore, it is recommended that such patients also be started on lower doses of ketoprofen capsules and closely monitored.

Rheumatoid Arthritis and Osteoarthritis
The recommended starting dose of ketoprofen capsules in otherwise healthy patients is 75 mg three times or 50 mg four times a day. Smaller doses of ketoprofen capsules should be utilized initially in small individuals or in debilitated or elderly patients. The recommended maximum daily dose of ketoprofen capsules is 300 mg/day.
Dosages higher than 300 mg/day of ketoprofen capsules are not recommended because they have not been studied. Concomitant use of ketoprofen capsules and ketoprofen extended-release capsules is not recommended. Relatively smaller people may need smaller doses.
As with other non-steroidal anti-inflammatory drugs, the predominant adverse effects of ketoprofen are gastrointestinal. To attempt to minimize these effects, physicians may wish to prescribe that ketoprofen capsules be taken with antacids, food, or milk. Although food delays the absorption of ketoprofen capsules (see CLINICAL PHARMACOLOGY), in most of the clinical trials ketoprofen was taken with food or milk.
Physicians may want to make specific recommendations to patients about when they should take ketoprofen capsules in relation to food and/or what patients should do if they experience minor GI symptoms associated with ketoprofen capsules.

Management of Pain and Dysmenorrhea
The usual dose of ketoprofen capsules recommended for mild-to-moderate pain and dysmenorrhea is 25 to 50 mg every 6 to 8 hours as necessary. A smaller dose should be utilized initially in small individuals, in debilitated or elderly patients, or in patients with renal or liver disease (see PRECAUTIONS). A larger dose may be tried if the patient’s response to a previous dose was less than satisfactory, but doses above 75 mg have not been shown to give added analgesia. Daily doses above 300 mg are not recommended because they have not been adequately studied. Because of its typical non-steroidal anti-inflammatory drug-side-effect profile, including as its principal adverse effect GI side effects (see WARNINGS and ADVERSE REACTIONS), higher doses of ketoprofen capsules should be used with caution and patients receiving them observed carefully.

HOW SUPPLIED

Ketoprofen capsules USP are available as follows:
25 mg: Dark green color cap and body, size “4” imprinted with “KETO 25” on cap with an edible white ink containing white to off-white crystalline powder supplied as:NDC 0276-0504-10 Bottles of 100

50 mg: Light green color cap and body, size “1” imprinted with “KETO 50” on cap with an edible
blue ink and containing white to off-white crystalline powder supplied as:
Bottles of 100 NDC 0276-0506-10
75 mg: White color cap and body, size “1” imprinted with “KETO 75” on cap with an edible blue
ink and containing white to off-white crystalline powder supplied as:

Bottles of 100 NDC 0276-0507-10

Keep tightly closed.

Store at 20° to 25°C (68° to 77°F) [See USP Controlled Room Temperature].

Dispense in a tight, light-resistant container as defined in the USP, with a child-resistant closure (as required).

Manufactured for:
Misemer Pharmaceuticals, Inc.
Ripley, MS 38663
Revised: 09/2021

MEDICATION GUIDE

Medication Guide for Non-Steroidal Anti-Inflammatory Drugs (NSAIDs)
Rx only

(See the end of this Medication Guide for a list of prescription NSAID medicines.)
What is the most important information I should know about medicines called Non-Steroidal Anti-Inflammatory Drugs (NSAIDs)?
NSAIDs can cause serious side effects, including:
• Increased risk of a heart attack or stroke that can lead to death. This risk may happen early in treatment and may increase:
o with increasing doses of NSAIDs
o with longer use of NSAIDs

Do not take NSAIDs right before or after a heart surgery called a “coronary artery bypass graft (CABG).”
Avoid taking NSAIDs after a recent heart attack, unless your healthcare provider tells you to. You may have an increased risk of another heart attack if you take NSAIDs after a recent heart attack.
• Increased risk of bleeding, ulcers, and tears (perforation) of the esophagus (tube leading from the mouth to the stomach), stomach and intestines:
o anytime during use
o without warning symptoms
o that may cause death
The risk of getting an ulcer or bleeding increases with:
o past history of stomach ulcers, or stomach or intestinal bleeding with use of NSAIDs
o taking medicines called “corticosteroids” and “anticoagulants”, “SSRIs”, or “SNRIs”
o increasing doses of NSAIDS
o longer use of NSAIDs
o smoking
o drinking alcohol
o older age
o poor health
o advanced liver disease
o bleeding problems

NSAIDs should only be used:
o exactly as prescribed
o at the lowest dose possible for your treatment
o for the shortest time needed

What are NSAIDs?
NSAIDs are used to treat pain and redness, swelling, and heat (inflammation) from medical conditions such as different types of arthritis, menstrual cramps and other types of short-term pain.

Who should not take NSAIDs?
Do not take NSAIDs:
• if you have had an asthma attack, hives, or other allergic reaction with aspirin or any other NSAIDs
• right before or after heart bypass surgery

Before taking NSAIDs, tell your healthcare provider about all of your medical conditions, including if you:
• have liver or kidney problems
• have high blood pressure
• have asthma
• are pregnant or plan to become pregnant. Taking NSAIDs at about 20 weeks of
pregnancy or later may harm your unborn baby. If you need to take NSAIDs for more
than 2 days when you are between 20 and 30 weeks of pregnancy, your healthcare
provider may need to monitor the amount of fluid in your womb around your baby. You
should not take NSAID after about 30 weeks of pregnancy.
• Are breastfeeding or plan to breast feed.

Tell your healthcare provider about all of the medicines you take, including
prescription or over-the-counter medicines, vitamins or herbal supplements. NSAIDs
and some other medicines can interact with each other and cause serious side effects. Do
not start taking any new medicine without talking to your healthcare provider first.
NSAIDs can cause serious side effects, including:
See “What is the most important information I should know about medicines called Nonsteroidal Anti-inflammatory Drugs (NSAIDs)?
• new or worse high blood pressure
• heart failure
• liver problems including liver failure
• kidney problems including kidney failure
• low red blood cells (anemia)
• life-threatening skin reactions
• life-threatening allergic reactions
• Other side effects of NSAIDs include: stomach pain, constipation, diarrhea, gas, heartburn, nausea, vomiting, and dizziness

Get emergency help right away if you have any of the following symptoms:
• shortness of breath or trouble breathing
• chest pain
• weakness in one part or side of your body
• slurred speech
• swelling of the face or throat

Stop your NSAID medicine and call your healthcare provider right away if you have any of the following symptoms:
• nausea
• more tired or weaker than usual
• diarrhea
• itching
• your skin or eyes look yellow
• indigestion or stomach pain
• flu-like symptoms
• vomit blood
• there is blood in your bowel movement or it is black and sticky like tar
• unusual weight gain
• skin rash or blisters with fever
• swelling of the arms and legs, hands and feet

If you take too much of your NSAID, call your healthcare provider or get medical help right away.
These are not all the side effects of NSAIDs. For more information, ask your healthcare provider or pharmacist about NSAIDs.
Call your doctor for medical advice about side effects. You may report side effects to FDA at 1-800-FDA-1088.

Other information about NSAIDs
• Aspirin is an NSAID but it does not increase the chance of a heart attack. Aspirin can cause bleeding in the brain, stomach, and intestines. Aspirin can also cause ulcers in the stomach and intestines.
• Some NSAIDs are sold in lower doses without a prescription (over-the-counter). Talk to your healthcare provider before using over-the-counter NSAIDs for more than 10 days.

General information about the safe and effective use of NSAIDs
Medicines are sometimes prescribed for purposes other than those listed in a Medication Guide. Do not use NSAIDs for a condition for which it was not prescribed. Do not give NSAIDs to other people, even if they have the same symptoms that you have. It may harm them.
If you would like more information about NSAIDs, talk with your healthcare provider. You can ask your pharmacist or healthcare provider for information about NSAIDs that is written for health professionals.

Dispense with Medication Guide available at:
https://misemerrx.com/products/ketoprofen

Manufactured for:
Misemer Pharmaceutical, Inc
Ripley, MS 38663

This Medication Guide has been approved by the U.S. Food and Drug Administration.
51UMS0000004US01
Revised: 09/2021